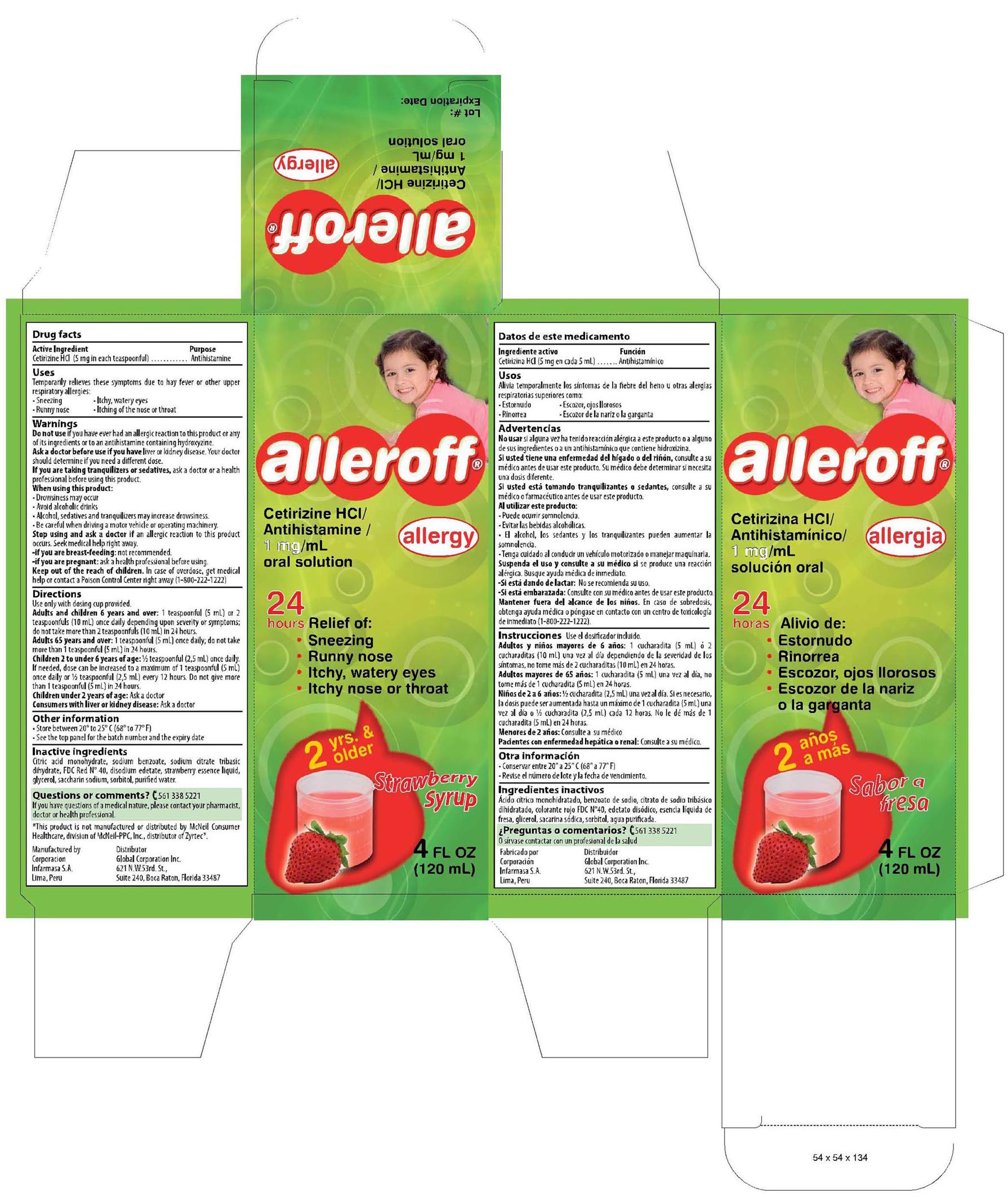 DRUG LABEL: ALLEROFF
NDC: 16853-1261 | Form: SYRUP
Manufacturer: Corporacion Infarmasa
Category: otc | Type: HUMAN OTC DRUG LABEL
Date: 20100115

ACTIVE INGREDIENTS: CETIRIZINE HYDROCHLORIDE 1 mg/1 1
INACTIVE INGREDIENTS: CITRIC ACID MONOHYDRATE 0.080 mg/1 1; SODIUM BENZOATE 0.100 mg/1 1; SODIUM CITRATE  0.090 mg/1 1; FD&C RED NO. 40 0.003 mg/1 1; EDETATE DISODIUM 0.025 mg/1 1; GLYCERIN 25 mg/1 1; SACCHARIN SODIUM 0.075 mg/1 1; SORBITOL 30 mg/1 1; WATER 100 mL/1 1; STRAWBERRY 0.07 mg/1 1

Drug Facts

ACTIVE INGREDIENT

(in each 5 ml teaspoonful) Cetirizine HCL 5 mg..........Antihistamine

Ask a doctor before use if you have
liver or kidney disease. Your doctor should determine if you need a different
dose.

Ask a doctor or pharmacist before use if you are taking tranquilizers or sedatives.
When using this product:

- Drowsiness may occur
- Avoid alcoholic drinks
- Alcohol, sedatives and tranquilizers may increase drowsiness
- Be careful when driving a motor vehicle or operating machinery

Do not use if you have ever had an allergic reaction to this product or any of its ingredients or to an antihistamine containing hidroxyzine

KEEP OUT OF REACH OF CHILDREN

In case of overdose, get medical help or contact a Poison Control Center right away. (1-800-222-1222)

If pregnant or breast feeding:

- if breast feeding: not recommended
- if pregnant: ask a health professional before use

Stop use and ask a doctor if an allergic reaction to this product occurs. Seek medical help right away.

Uses
Temporarily relieves these symptoms due to hay fever or other upper respiratory allergies:

- Runny Nose
- Itchy,water eyes
- Itching of the nose or throat
- Sneezing

QUESTIONS

If you have questions of a medical nature, please contact your pharmacist, doctor or health care profesional

Questions or comments? 561 338 5221

STORAGE AND HANDLING

Store between 20ºC to 25ºC (68ºF to 77ºF)

See bottom panel for lot number and expiration date

DOSAGE AND ADMINISTRATION

Use only with enclosed dosing cup

Adults and Children 6 years and over 1 teaspoonful (5ml) ot 2 teaspoonful (10ml) once daily depending upon severity of symptoms; do not take more than 2 teaspoonful (10ml) in 24 hours

Adults 65 years and over 1 teaspoonful (5ml) once daily; do not take more than 1 teaspoonful (5ml) in 24 hours

Children 2 to under 6 years of age 1/2 teaspoonful (2.5ml) once daily.If needed, dose can be increased to a maximum of 1 teaspoon (5ml) once daily or 1/2 teaspoonful (2.5ml) every 12 hours. Do not give more than 1 teaspoonful (5ml) in 24 hours

Children under 2 years of age Ask a Doctor

Consumer with liver or kidney disease Ask a Doctor

INACTIVE INGREDIENT

Citric and monohydrate, Sodium Benzoate, Sodium Citrate Tribasic Dihydrate, FDC Red Nº 40, Disodium Edetate, Strawberry Essence Liquid, Glycerol, Saccharin Sodium, Sorbitol, Purified Water

PACKAGE LABEL

Enter section text here